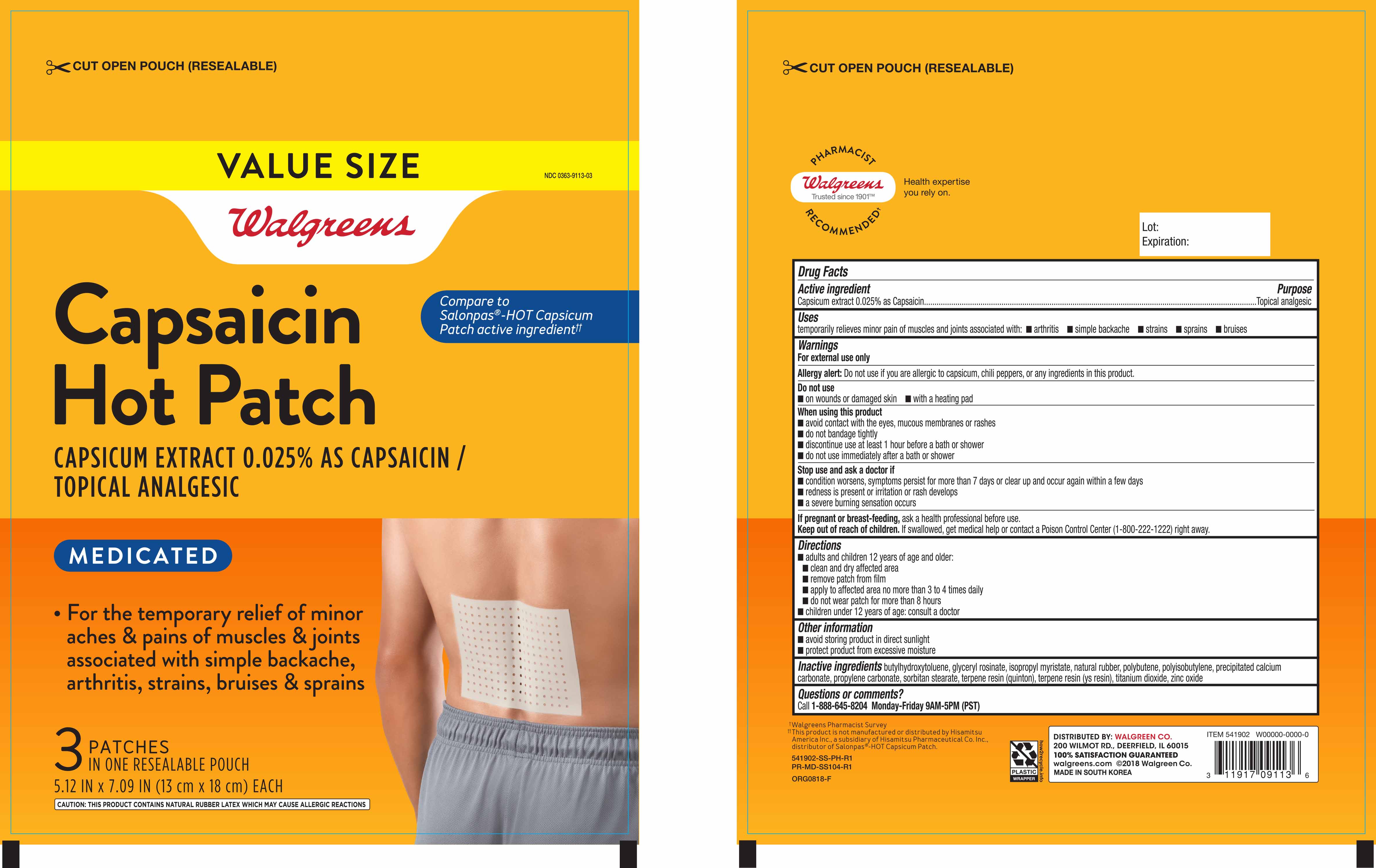 DRUG LABEL: Walgreens Capsaicin Hot
NDC: 0363-9113 | Form: PATCH
Manufacturer: Walgreen Co
Category: otc | Type: HUMAN OTC DRUG LABEL
Date: 20181204

ACTIVE INGREDIENTS: CAPSAICIN 0.6 mg/1 1
INACTIVE INGREDIENTS: CALCIUM CARBONATE; GLYCERYL ROSINATE; POLYISOBUTYLENE (1100000 MW); POLYBUTENE (1400 MW); BUTYLATED HYDROXYTOLUENE; ISOPROPYL MYRISTATE; NATURAL LATEX RUBBER; PROPYLENE CARBONATE; SORBITAN MONOSTEARATE; TITANIUM DIOXIDE; ZINC OXIDE

Walgreens Capsaicin Patch 3ct/resealable pouch (541902, 2018)

Active ingredient Purpose

Capsaicin extract 0.025% as Capsaicin.....................................Topical Analgesic

PURPOSE

Uses Temporarily relieves minor pain associated with:

- arthritis
- simple backache
- strains
- sprains
- bruises

Warnings

- For external use only
- Allergy alert: Do not use if you are allergic to capsicum, chili peppers, or any ingredients in this product.

Do not use

- on wounds or damaged skin
- with a heating pad

When using this product

- avoid contact with the eyes, mucous membranes or rashes
- do not bandage tightly
- discontinue use at least 1 hour before a bath or shower
- do not use immediately after a bath or shower

Stop use and ask a doctor if

- conditions worsens, symptoms persist more than 7 days or clear up and occur again within a few days
- redness is present or irritation or rash develops
- a severe burining sensation occurs

PREGNANCY OR BREAST FEEDING

If pregnant or breast-feeding, ask a healthcare professional before use.

Keep out of reach of children. If swallowed, get medical help or contact a Poison Control Center (1-800-222-1222) right away.

Directions

- adults and children 12 years of age and older:
- clean and dry affected area
- remove patch from film
- apply to affected area no more than 3 to 4 times daily
- do not wear patch for more than 8 hours
- children under 12 years of age: consult a doctor

Other information

- avoid storing product in direct sunlight
- protect product from excessive moisture

INACTIVE INGREDIENT

butylhydroxytoluene, glyceryl rosinate, isopropyl myristate, natural rubber, polybutene, polyisobutylene, precipitated calcium carbonate, propylene carbonate, sorbitan stearate, terpene resin (quinton), terpene resin (ys resin), titanium dioxide, zinc oxide

Questions or comments?

Call 1-888-645-8204 Monday-Friday 9AM-5PM (PST)

DOSAGE AND ADMINISTRATION

Distributed By:

Walgreen Co

200 Wilmot Rd.

Deerfield, IL 60005

Made in South Korea